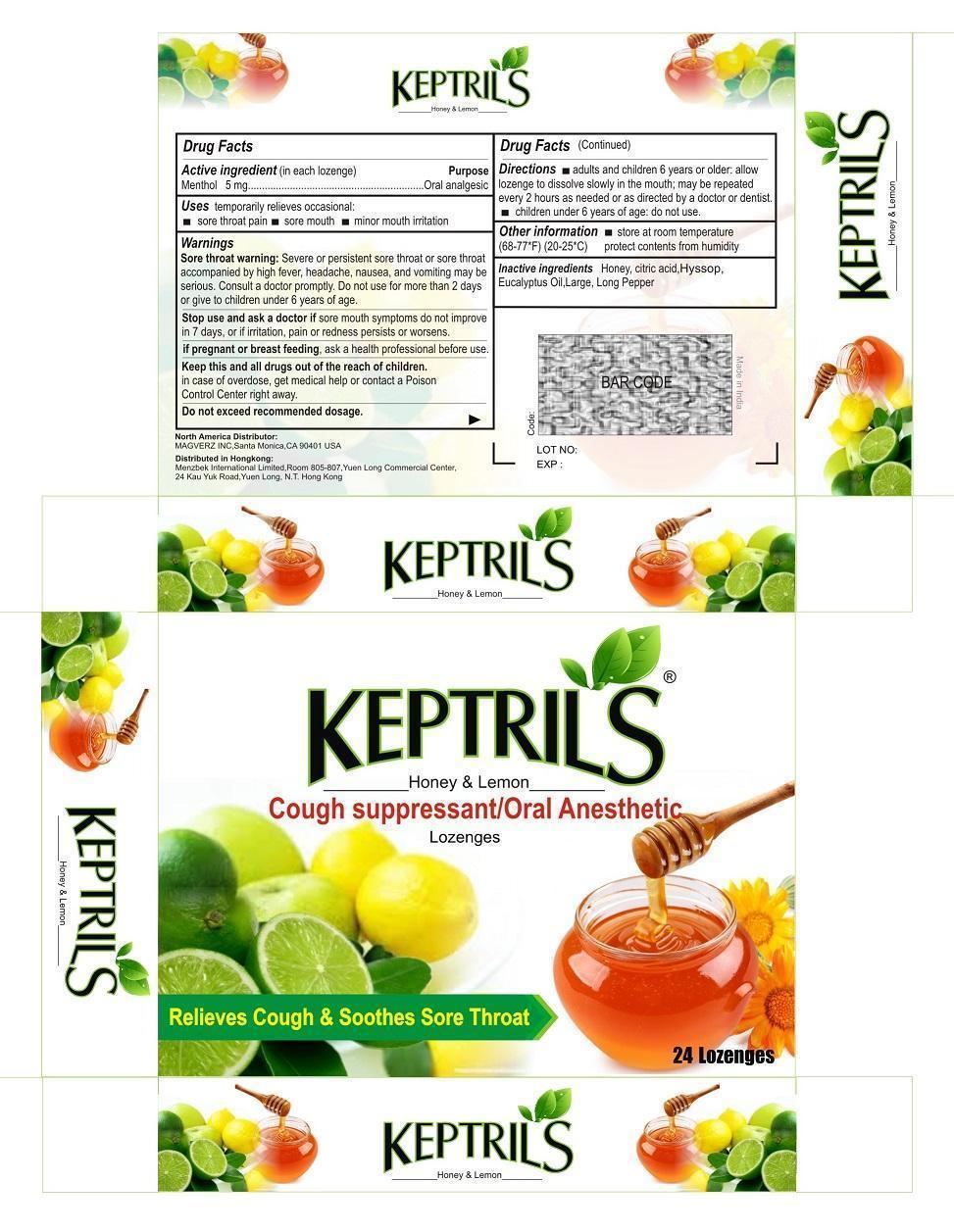 DRUG LABEL: KEPTRILS
NDC: 59240-004 | Form: LOZENGE
Manufacturer: MAGVERZ INC
Category: otc | Type: HUMAN OTC DRUG LABEL
Date: 20150904

ACTIVE INGREDIENTS: MENTHOL 5 mg/1 1
INACTIVE INGREDIENTS: HONEY; CITRIC ACID MONOHYDRATE; HYSSOP OIL; EUCALYPTUS OIL; LONG PEPPER

Keptril

Actives

Menthol 5mg in each Lozenge

Inactives

Honey, Citric Acid, Hyssop,Eucalyptus oil, Long pepper

Purpose

Oral Analgesic

Uses

Sore throat pain

Sore mouth

Minor mouth irritation

Directions

Adults and childrens 6 years older: allow lozene to dissolve slowly in the mouth; may be repeated every two hours as nedded or as directed by doctor or dentist .

Childrens under 6 years of age; do not use.

Warnings

Sore throat warninings : Server or persistent sore throat or sore throat accomapnied by high fever headache,nausea and vomittin may be serious. Consult a doctor promptly. Do not use for more than two days or gice to children under 6 years of age.

Keep out of reach of children

Keep this and all drugs out of reach of children